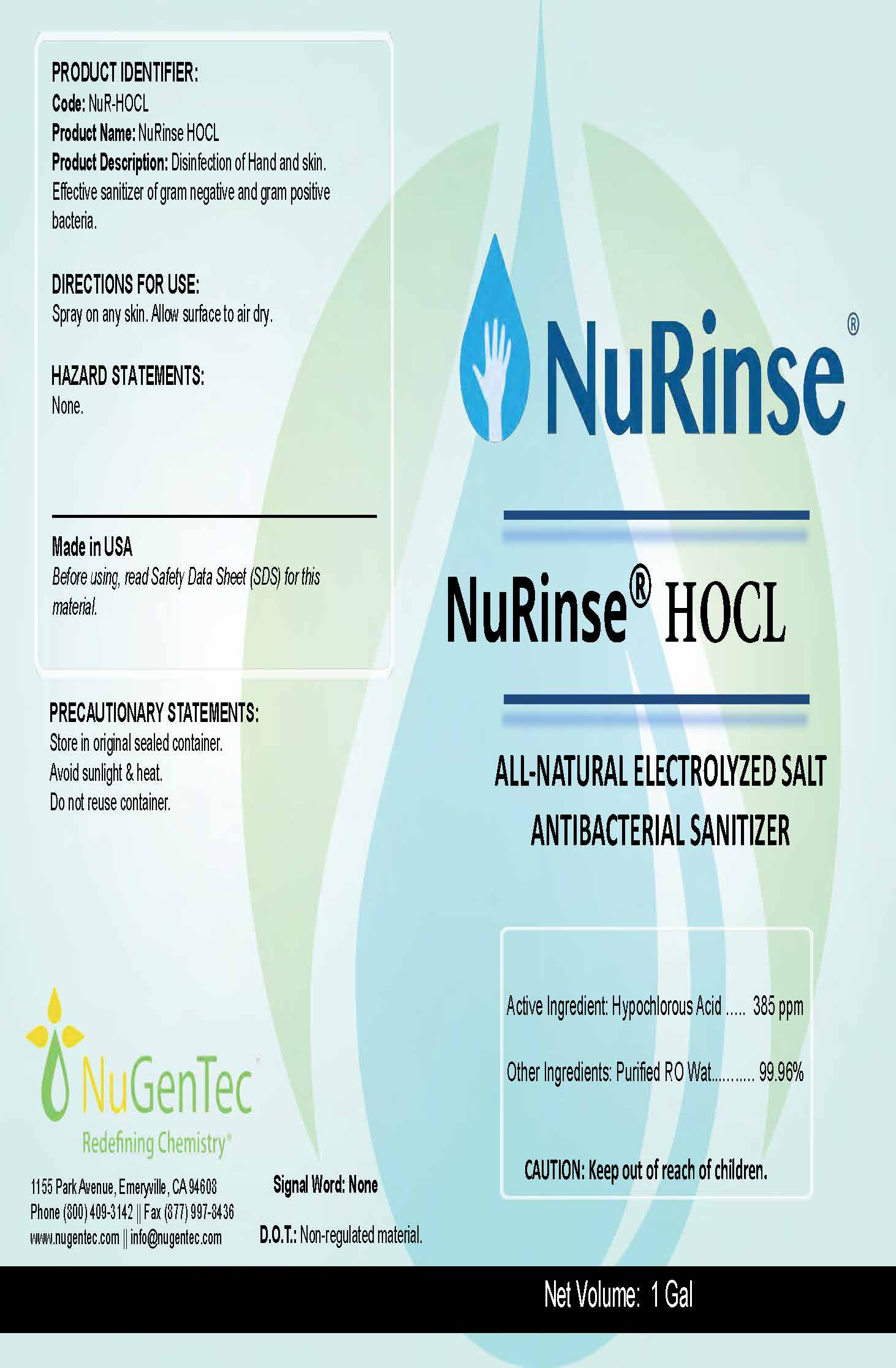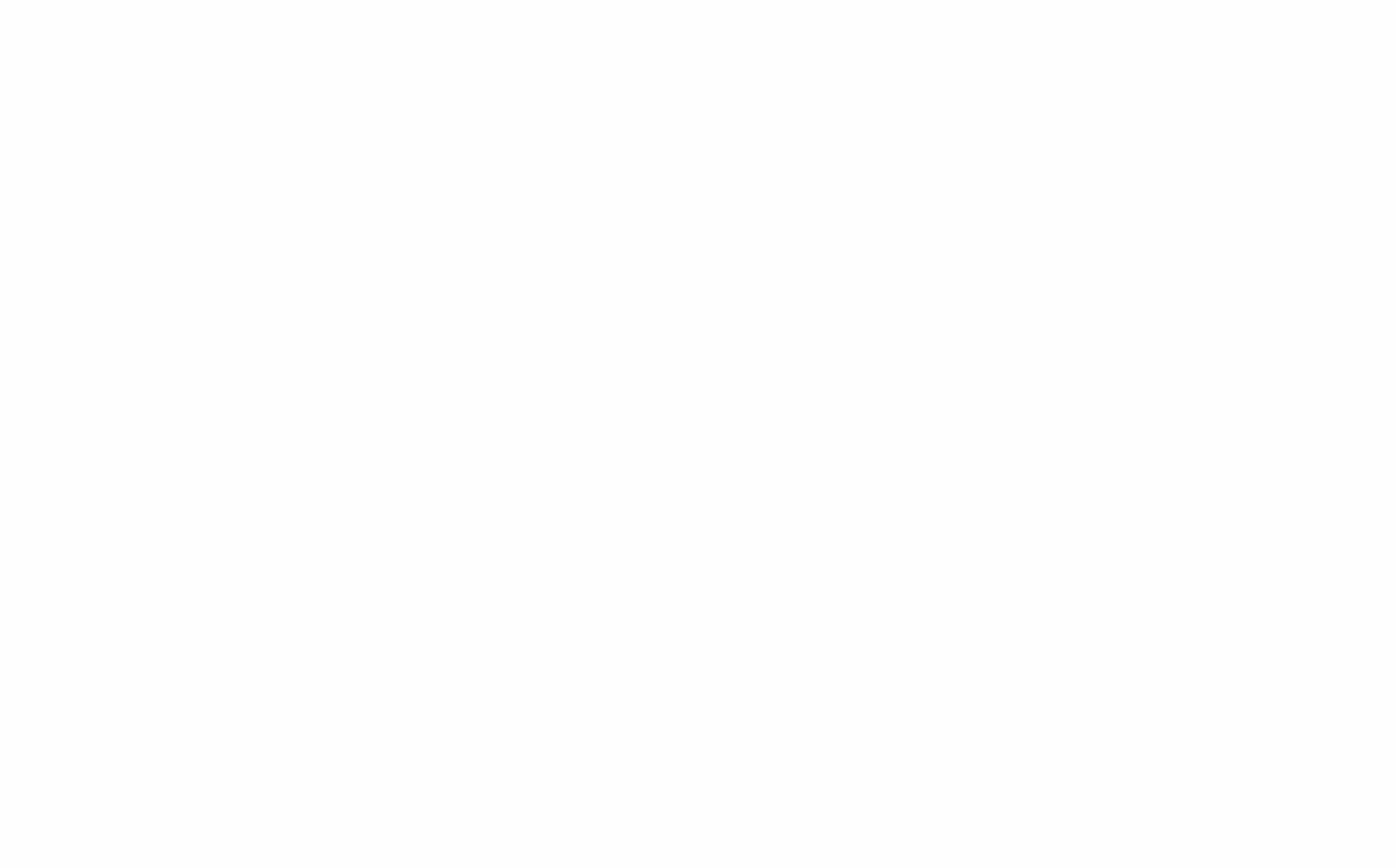 DRUG LABEL: NuRinse
NDC: 77368-385 | Form: LIQUID
Manufacturer: NuGenTec
Category: otc | Type: HUMAN OTC DRUG LABEL
Date: 20221222

ACTIVE INGREDIENTS: HYPOCHLOROUS ACID 0.000385 g/100 mL
INACTIVE INGREDIENTS: WATER

NuRinse Hand Sanitizer

The hand sanitizer is manufactured using only the following United States Pharmacopoeia (USP) grade ingredients in the preparation of the product (percentage in final product formulation) consistent with World Health Organization (WHO) recommendations:

1. HOCL 385ppm
2. Sterile distilled water or boiled cold water.

The firm does not add other active or inactive ingredients. Different or additional ingredients may impact the quality and potency of the product.

HOCl solutions are already included in the WHO list of coronavirus-effective biocides, and in the US EPA ‘N’ list of disinfecting agents able to control emerging pathogens like SARS-CoV-2. 37,126 More than ten branded aqueous HOCl formulations have been cleared by the US FDA for topical use in wound management over the last decade. A Class III medical product approval for HOCl has been granted in the EU, and the Japanese Ministry of Health has approved use of HOCl for topical medical applications. The US FDA has approved HOCl for high level disinfection and sterilization of medical instruments, including those for use at critical (i.e., sterile) sites

Active Ingredient(s)

HOCL 385ppm Purpose: Antiseptic

Purpose

Antiseptic, Hand Sanitizer

Use

Hand Sanitizer to help reduce bacteria that potentially can cause disease. For use when soap and water are not available.

Warnings

None

Stop use and ask a doctor if irritation or rash occurs. These may be signs of a serious condition.

Keep out of reach of children.

Directions

- Place enough product on hands to cover all surfaces. Rub hands together until dry.
- Supervise children under 6 years of age when using this product.

Other information

- Store between 15-30C (59-86F)
- Avoid freezing and excessive heat above 40C (104F)
- Avoid Direct Sunlight, store in an opaque bottle.
- Keep sealed when not in use.

Inactive ingredients

Purified water USP

Package Label - Principal Display Panel

3785 mL NDC: 77368-385-01